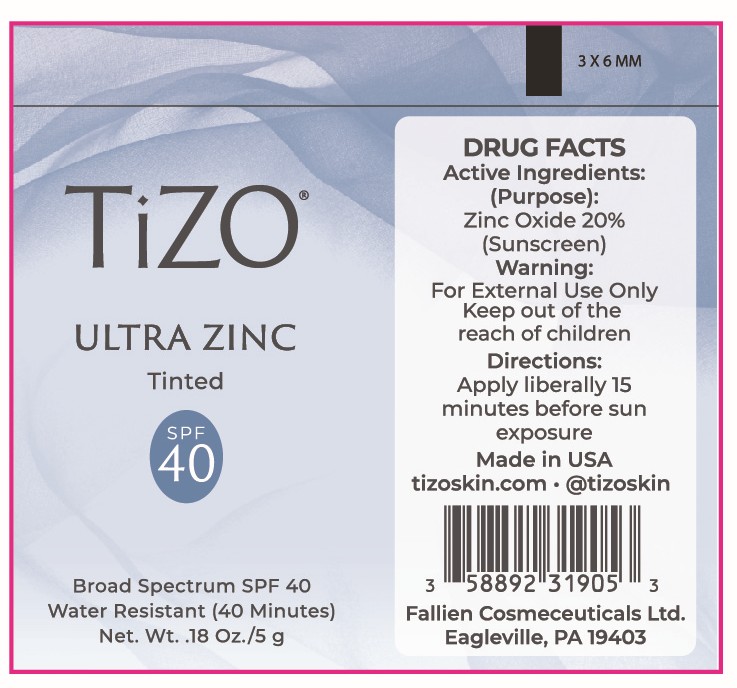 DRUG LABEL: TiZO Ultra Zinc SPF 40 (Tinted)
NDC: 58892-319 | Form: CREAM
Manufacturer: Fallien Cosmeceuticals, LTD.
Category: otc | Type: HUMAN OTC DRUG LABEL
Date: 20250203

ACTIVE INGREDIENTS: ZINC OXIDE 200 mg/1 g
INACTIVE INGREDIENTS: GLYCERIN; HYDROGEN DIMETHICONE (20 CST); SODIUM CHLORIDE; TRIETHANOLAMINE; CETYL PEG/PPG-10/1 DIMETHICONE (HLB 4); CYCLOPENTASILOXANE; MICROCRYSTALLINE WAX; MICA; C12-15 ALKYL BENZOATE; POLYHYDROXYSTEARIC ACID (2300 MW); ALPHA-TOCOPHEROL ACETATE; TETRAHEXYLDECYL ASCORBATE; POLYSORBATE 20; CAPRYLYL GLYCOL; DIMETHICONE CROSSPOLYMER; POLYGLYCERYL-4 ISOSTEARATE; DIMETHICONE/VINYL DIMETHICONE CROSSPOLYMER (SOFT PARTICLE); IRON OXIDES; BISMUTH OXYCHLORIDE; TRIETHOXYCAPRYLYLSILANE; WATER; STEARYL DIMETHICONE (400 MPA.S AT 50C); CYCLOHEXASILOXANE; DIMETHICONE; PEG-10 DIMETHICONE (600 CST); PEG-30 DIPOLYHYDROXYSTEARATE; CAPRYLHYDROXAMIC ACID; DIMETHICONOL (2000 CST); EDETATE DISODIUM ANHYDROUS

Active Ingredients:

Zinc Oxide 20%

Purpose:

Sunscreen

Directions:

Apply liberally 15 minutes before sun exposure.

Warnings:

For external use only. Keep out of the reach of children

Warnings and Directions:

For external use only. Keep out of the reach of children. Apply liberally 15 minutes before sun exposure.

INACTIVE INGREDIENT

Bismuth Oxychloride, C12-15 Alkyl Benzoate, Caprylhydroxamic Acid, Caprylyl Glycol, Cetyl PEG/PPG-10/1 Dimethicone, Cyclohexasiloxane, Cyclopentasiloxane, Dimethicone, Dimethicone Crosspolymer, Dimethicone/Vinyl Dimethicone Crosspolymer, Dimethiconol, Disodium EDTA, Glycerin, Hydrogen Dimethicone, Iron Oxides, Mica, Microcrystalline Wax, PEG-10 Dimethicone, PEG-30 Dipolyhydroxystearate, Polyglyceryl-4 Isostearate, Polyhydroxystearic Acid, Polysorbate 20, Sodium Chloride, Stearyl Dimethicone, Tetrahexyldecyl Ascorbate, Tocopheryl Acetate, Triethanolamine, Triethoxycaprylylsilane, Water

Warning:

Keep out of the reach of children.